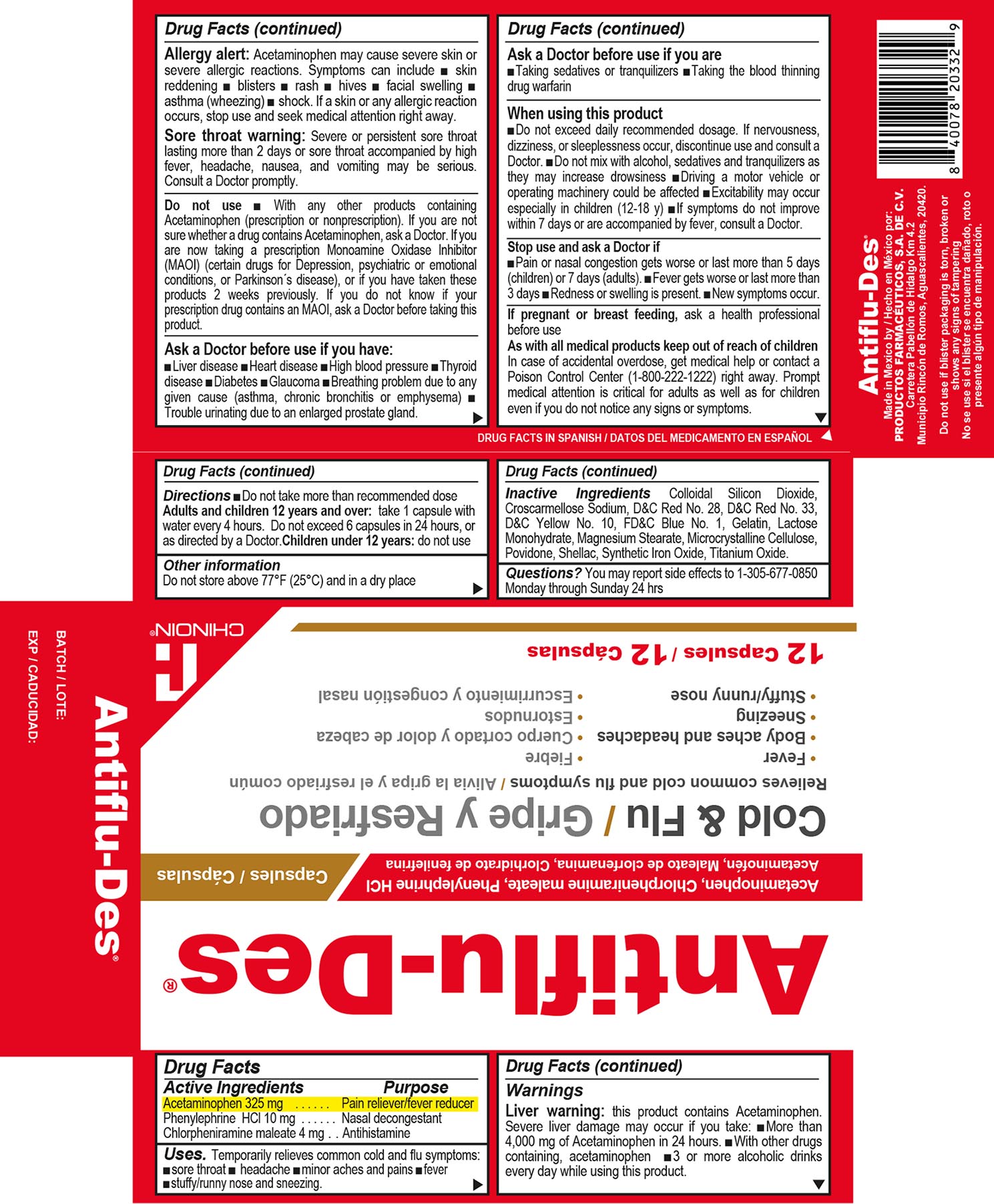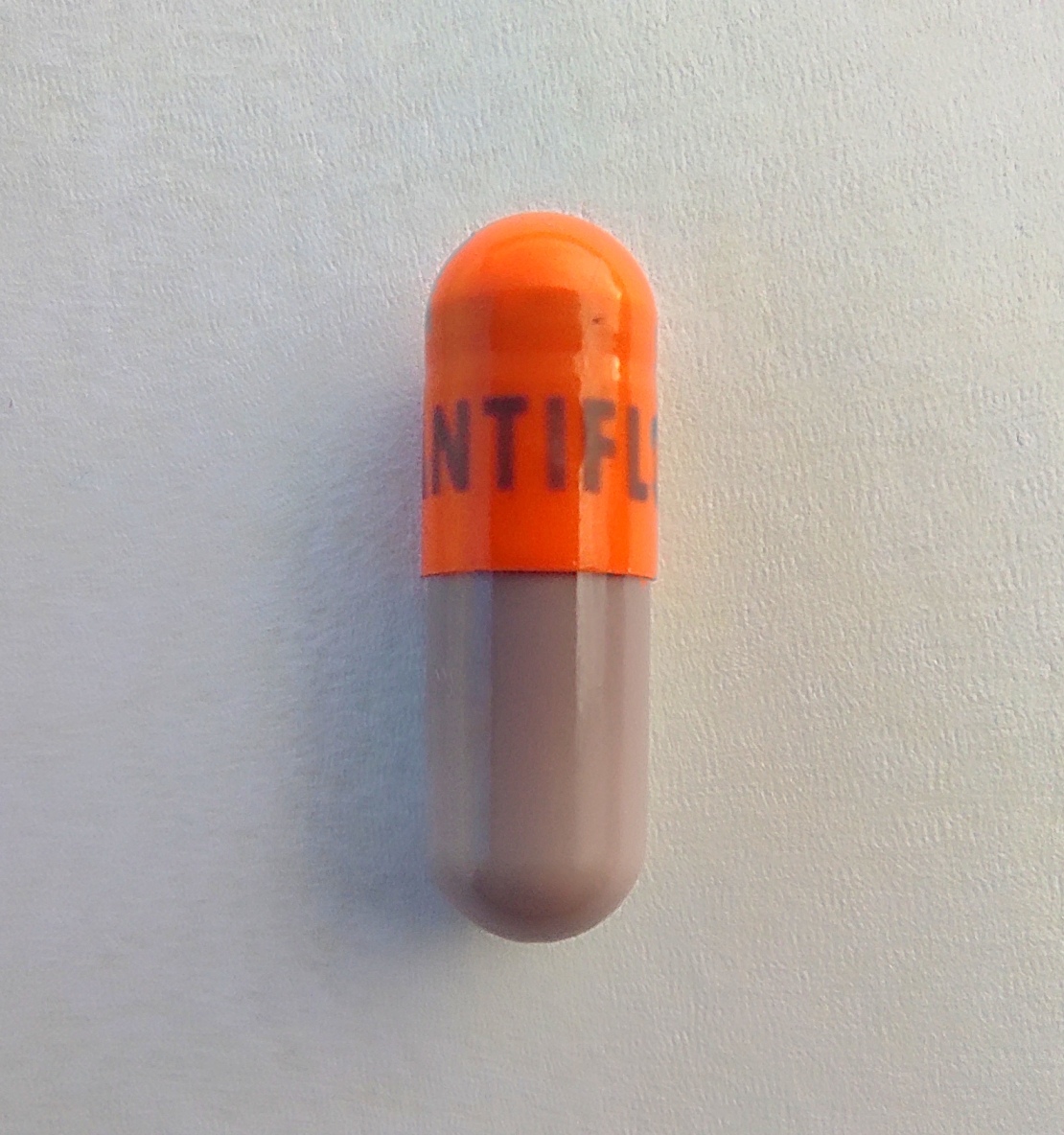 DRUG LABEL: Antiflu Des
NDC: 82688-001 | Form: CAPSULE
Manufacturer: Productos Farmaceuticos, S.A. de C.V.
Category: otc | Type: HUMAN OTC DRUG LABEL
Date: 20241017

ACTIVE INGREDIENTS: ACETAMINOPHEN 325 mg/1 1; PHENYLEPHRINE HYDROCHLORIDE 10 mg/1 1; CHLORPHENIRAMINE MALEATE 4 mg/1 1
INACTIVE INGREDIENTS: MICROCRYSTALLINE CELLULOSE; MAGNESIUM STEARATE; GELATIN; CROSCARMELLOSE SODIUM; D&C RED NO. 28; D&C RED NO. 33; POVIDONE; FD&C BLUE NO. 1; LACTOSE MONOHYDRATE; D&C YELLOW NO. 10; SILICON DIOXIDE; TITANIUM DIOXIDE; SHELLAC; FERRIC OXIDE RED

AntiDesCldFluCaps

Active Ingredients

Acetaminophen 325 mg

Phenylephrine HCl 10 mg

Chlorpheniramine Maleate 4 mg

Purpose

Pain reliever/fever reducer

Nasal decongestant

Antihistamine

Uses

Temporarily relieves common cold and flu symptoms: ▪sore throat ▪headache ▪minor aches and pains ▪fever ▪stuffy/runny nose and sneezing

Warnings

Liver warning This product contains acetaminophen. Severe liver damage may occur if you take ▪More than 4,000 mg in 24 hours, which is the maximum daily amount ▪ With other drugs containing acetaminophen ▪ 3 or more alcoholic drinks every day while using this product.

Allergy alert: Acetaminophen may cause severe skin or severe allergic reactions. Symptoms can include▪ skin reddening ▪ blisters ▪ rash ▪ hives ▪ facial swelling ▪ asthma (wheezing) ▪ shock. If a skin or any allergic reaction occurs, stop use and seek medical attention right away.

Sore throat warning: Severe or persistent sore throat lasting more than 2 days or sore throat accompanied by high fever, headache, nausea, and vomiting may be serious. Consult a Doctor promptly.

Do not use

▪ With any other drug containing acetaminophen (prescription or nonprescription). If you are not sure whether a drug contains Acetaminophen, ask a Doctor. If you are now taking a prescription Monoamine Oxidase Inhibitor (MAOI) (certain drugs for depression, psychiatric, or emotional conditions, or Parkinson's disease), or if you have taken these products 2 weeks previously. If you do not know if your prescription drug contains an MAOI, ask a Doctor before taking this product

Ask a Doctor before use if you have

▪ Liver disease ▪ Heart disease ▪ High blood pressure ▪ Thyroid disease ▪ Diabetes ▪Glaucoma ▪ Breathing problem due to any given cause (asthma, chronic bronchitis or emphysema) ▪ Trouble urinating due to an enlarged prostate gland

Ask a Doctor before use if you are

▪Taking sedatives or tranquilizers ▪Taking the blood thinning drug warfarin

When using this product

▪ Do not exceed recommended dosage. If nervousness, dizziness, or sleeplessness occur, discontinue use and consult a Doctor. ▪ Do not mix with alcohol, sedatives and tranquilizers as they may increase drowsiness ▪ Driving a motor vehicle or operating machinery could be affected ▪ Excitability may occur especially in children(12-18 y) ▪ if symptoms do not improve within 7 days or are accompanied by fever, consult a Doctor

Stop use and ask a Doctor if

▪ Pain, or nasal congestion gets worse or lasts more than 5 days (children) or 7 days (adults) ▪ Fever gets worse or last more than 3 days ▪ Redness or swelling is present ▪ New symptoms occur

Keep out of reach of children

If pregnant or breast-feeding, ask a health professional before use .

As with all medical products keep out of reach of children.

In case of accidental overdose, get medical help or contact a Poison Control Center (1-800-222-1222) right away. Prompt medical attention is critical for adults as well as for children even if you do not notice any signs or symptoms.

Directions

▪ Do not take more than recommended dose Adults and children 12 years of age and over: take 1 capsule with water every 4 hours. ▪ Do not exceed 6 capsules in 24 hours Children under 12 years of age: do not use

Other information

Do not store above 77ºF(25ºC) and in a dry place

Inactive Ingredients

Colloidal Silcon Dioxide, D&C Red No. 28, D&C Red No. 33, D&C Yellow No. 10, FD&C Blue No. 1, Gelatin, Lactose Monohdyrate, Magnesium Stearate, Microcrystalline Cellulose, Povidone, Shellac, Synthetic Iron Oxide, Titanium Dioxide

Questions and Comments?

You may report any side effects to 1-305-677-0850 Monday through Sunday 24 hrs